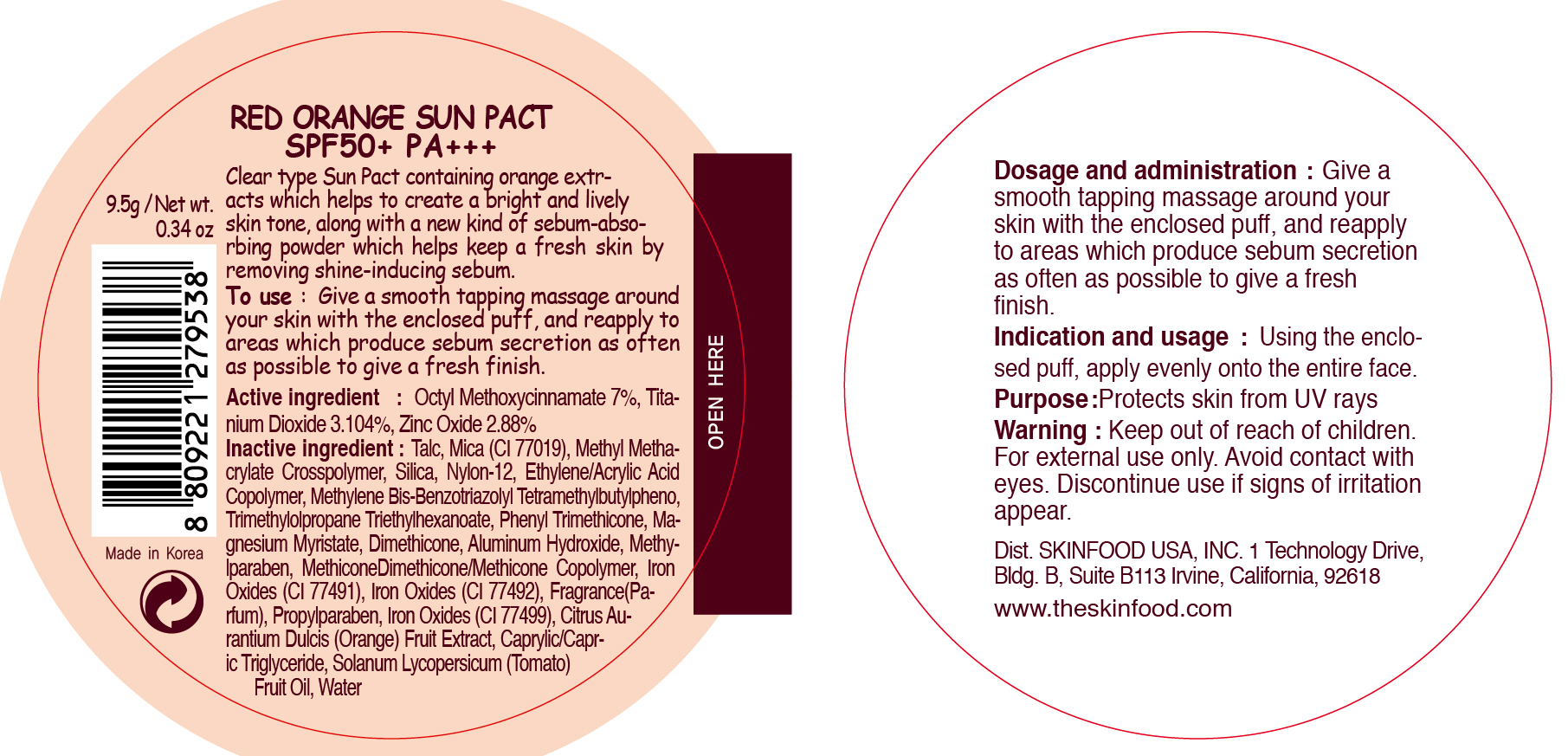 DRUG LABEL: RED ORANGE SUN PACT
NDC: 76214-037 | Form: POWDER
Manufacturer: SKINFOOD CO., LTD.
Category: otc | Type: HUMAN OTC DRUG LABEL
Date: 20111009

ACTIVE INGREDIENTS: OCTINOXATE 0.66 g/9.5 g; TITANIUM DIOXIDE 0.29 g/9.5 g; ZINC OXIDE 0.27 g/9.5 g
INACTIVE INGREDIENTS: WATER; TALC; MICA; SILICON DIOXIDE; TRIMETHYLOLPROPANE TRIETHYLHEXANOATE; PHENYL TRIMETHICONE; MAGNESIUM MYRISTATE; DIMETHICONE; ALUMINUM HYDROXIDE; METHYLPARABEN; PROPYLPARABEN; ORANGE; MEDIUM-CHAIN TRIGLYCERIDES; TOMATO

Drug Facts

ACTIVE INGREDIENT

Active ingredients: OCTINOXATE 7%, TITANIUM DIOXIDE 3.104%, ZINC OXIDE 2.88%

Inactive ingredients:
Talc, Mica (CI 77019), Methyl Methacrylate Crosspolymer, Silica, Nylon-12, Ethylene/Acrylic Acid Copolymer, Methylene Bis-Benzotriazolyl Tetramethylbutylpheno, Trimethylolpropane Triethylhexanoate, Phenyl Trimethicone, Magnesium Myristate, Dimethicone, Aluminum Hydroxide, Methylparaben, MethiconeDimethicone/Methicone Copolymer, Iron Oxides (CI 77491), Iron Oxides (CI 77492), Fragrance(Parfum), Propylparaben, Iron Oxides (CI 77499), Citrus Aurantium Dulcis (Orange) Fruit Extract, Caprylic/Capric Triglyceride, Solanum Lycopersicum (Tomato) Fruit Oil, Water

Purpose: Protects skin from UV rays.

Warnings:
For external use only.
Avoid contact with eyes.
Discontinue use if signs of irritation appear.

Keep out of reach of children:
Keep out of reach of children.

Indication and usage:
Using the enclosed puff, apply evenly onto the entire face.

Dosage and administration:
Give a smooth tapping massage around your skin with the enclosed puff, and reapply to areas which produce sebum secretion as often as possible to give a fresh finish.